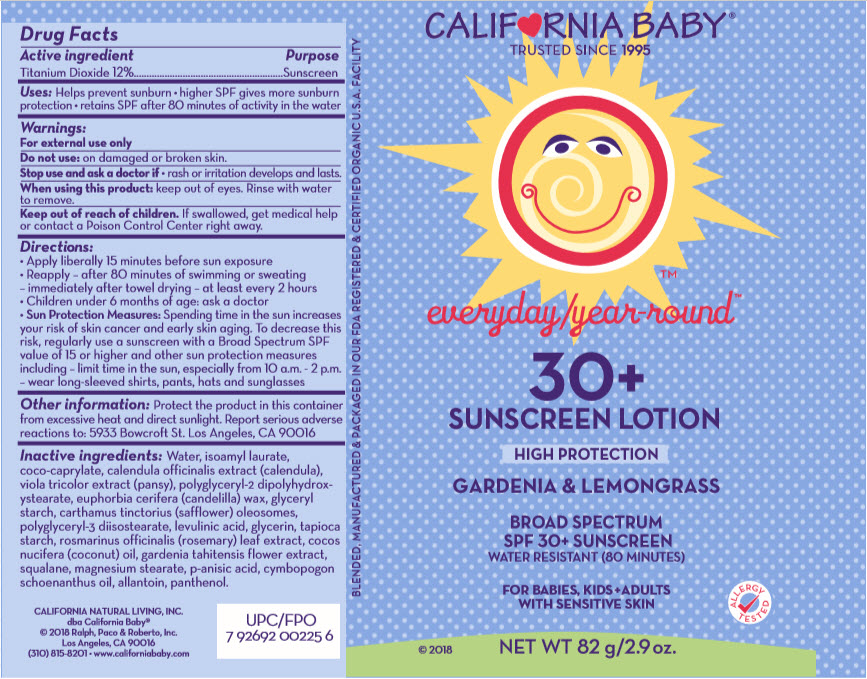 DRUG LABEL: SPF30 EVERYDAY/YEAR-ROUND SUNSCREEN
NDC: 52915-030 | Form: LOTION/SHAMPOO
Manufacturer: ORGANIC & SUSTAINABLE BEAUTY
Category: otc | Type: HUMAN OTC DRUG LABEL
Date: 20241107

ACTIVE INGREDIENTS: TITANIUM DIOXIDE 120 mg/1 g
INACTIVE INGREDIENTS: Water; isoamyl laurate; coco-caprylate; calendula officinalis flower; VIOLA TRICOLOR WHOLE; polyglyceryl-2 dipolyhydroxystearate; candelilla wax; starch, rice; carthamus tinctorius seed oleosomes; polyglyceryl-3 diisostearate; levulinic acid; medium-chain triglycerides; starch, tapioca; rosemary; coconut oil; squalane; magnesium stearate; p-anisic acid; allantoin; panthenol; gardenia taitensis flower; cymbopogon schoenanthus oil

SPF30 EVERYDAY/YR-ROUND™ SUNSCREEN LOTION

Drug Facts

Active ingredient

Titanium Dioxide 12%

Purpose

Sunscreen

Uses

- helps prevent sunburn
- higher SPF gives more sunburn protection
- retains SPF after 80 minutes of activity in the water

Warnings

For external use only

Do not use on damaged or broken skin.

Stop use and ask a doctor if

- rash occurs.

When using this product keep out of eyes. Rinse with water to remove.

Keep out of reach of children. If swallowed, get medical help or contact a Poison Control Center right away.

Directions:

- Apply liberally 15 minutes before sun exposure
- Reapply
  - after 80 minutes of swimming or sweating
  - immediately after towel drying
  - at least every 2 hours
- Children under 6 months: ask a doctor
- Sun Protection Measures: Spending time in the sun increases your risk of skin cancer and early skin aging. To decrease this risk, regularly use a sunscreen with a Broad Spectrum SPF value of 15 or higher and other sun protection measures including
  - limit time in the sun, especially from 10 a.m. - 2 p.m.
  - wear long-sleeved shirts, pants, hats and sunglasses

Other information

- protect the product in this container from excessive heat and direct sunlight
- report serious adverse reactions to: 5933 Bowcroft St. Los Angeles, CA 90016

Inactive ingredients

Water, isoamyl laurate, coco-caprylate, calendula officinalis extract (calendula), viola tricolor extract (pansy), polyglyceryl-2 dipolyhydroxystearate, euphorbia cerifera (candelilla) wax, glyceryl starch, carthamus tinctorius (safflower) oleosomes, polyglyceryl-3 diisostearate, levulinic acid, glycerin, tapioca starch, rosmarinus officinalis (rosemary) leaf extract, cocos nucifera (coconut) oil, gardenia tahitensis flower extract, squalane, magnesium stearate, p-anisic acid, cymbopogon schoenanthus oil, allantoin, panthenol.

PRINCIPAL DISPLAY PANEL - 82 g Tube Label

CALIF♥RNIA BABY®

TRUSTED SINCE 1995

everyday/year-round™

30+
SUNSCREEN LOTION
HIGH PROTECTION
GARDENIA & LEMONGRASS

BROAD SPECTRUM
SPF 30+ SUNSCREEN
WATER RESISTANT (80 MINUTES)

FOR BABIES, KIDS + ADULTS
WITH SENSITIVE SKIN

© 2018
NET WT 82 g/2.9 oz.

ALLERGY
TESTED